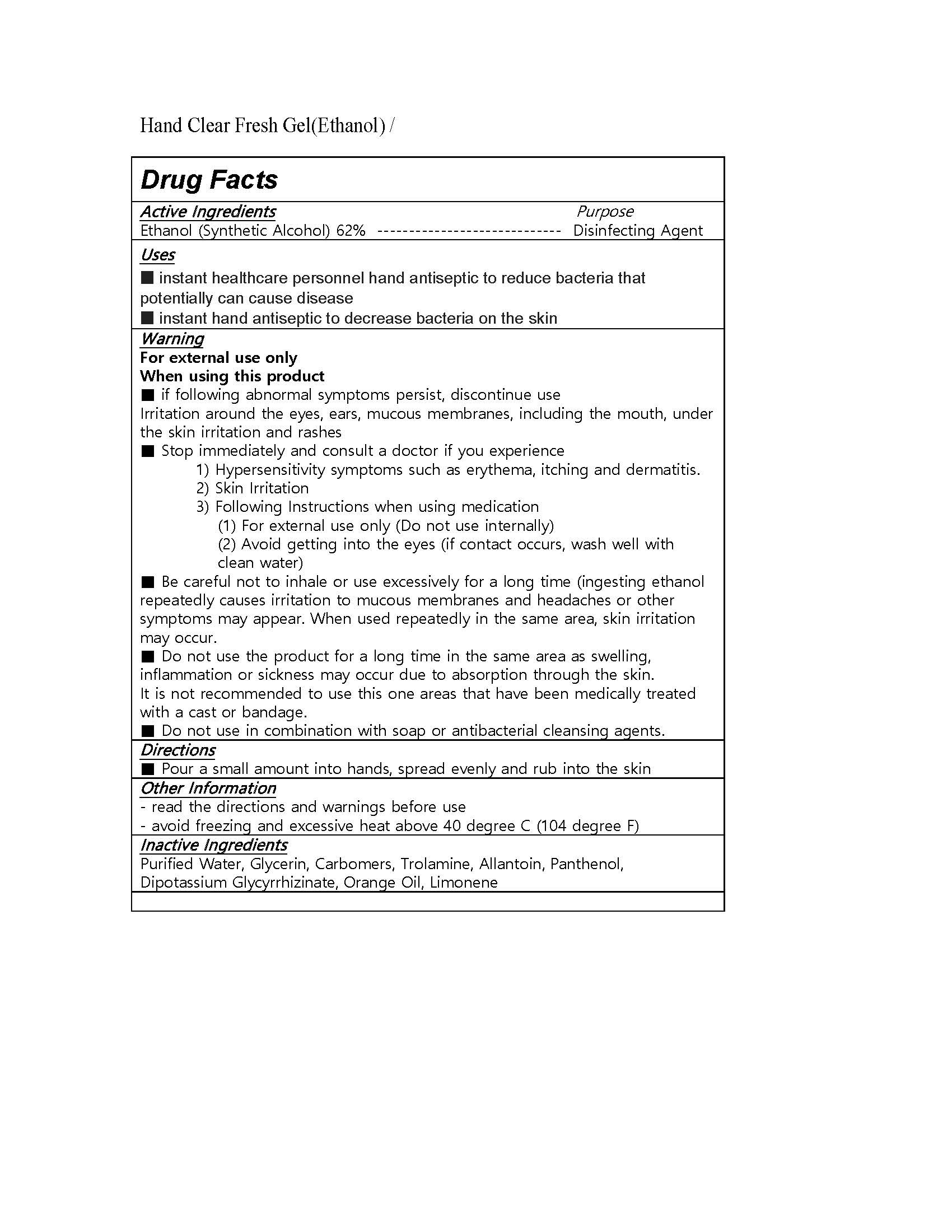 DRUG LABEL: MARVELOUS HAND SANITIZER
NDC: 74247-0005 | Form: GEL
Manufacturer: Rainbow Co Ltd
Category: otc | Type: HUMAN OTC DRUG LABEL
Date: 20200409

ACTIVE INGREDIENTS: ALCOHOL 70 g/100 mL
INACTIVE INGREDIENTS: PANTHENOL; BUTYLENE GLYCOL; ALOE VERA LEAF; CARBOMER 940; PEG-60 HYDROGENATED CASTOR OIL; TROLAMINE; WATER

Drug Facts

ACTIVE INGREDIENT

alcohol

INACTIVE INGREDIENT

Water, Carbomer, triethaneolamine, peg-60 hydrogenated castor oil, panthenol, butylene glycol, aloe barbadensis leaf extract

PURPOSE

to desrease bacteria on hands.

KEEP OUT OF REACH OF THE CHILDREN

INDICATIONS AND USAGE

Apply to clean, dry hands. Apply sufficient amount to thoroughly wet all surfaces of hands and fingers. Rub onto hands until dry.

Supervise children in the use of this product.

WARNINGS

■ Flammable. Keep away from fire or flame.

■ For external use only.

■ Do not use in eyes.

■ lf swallowed, get medical help promptly.

■ Stop use, ask doctor lf irritation occurs.

■ Keep out of reach of children.

DOSAGE AND ADMINISTRATION

for external use only